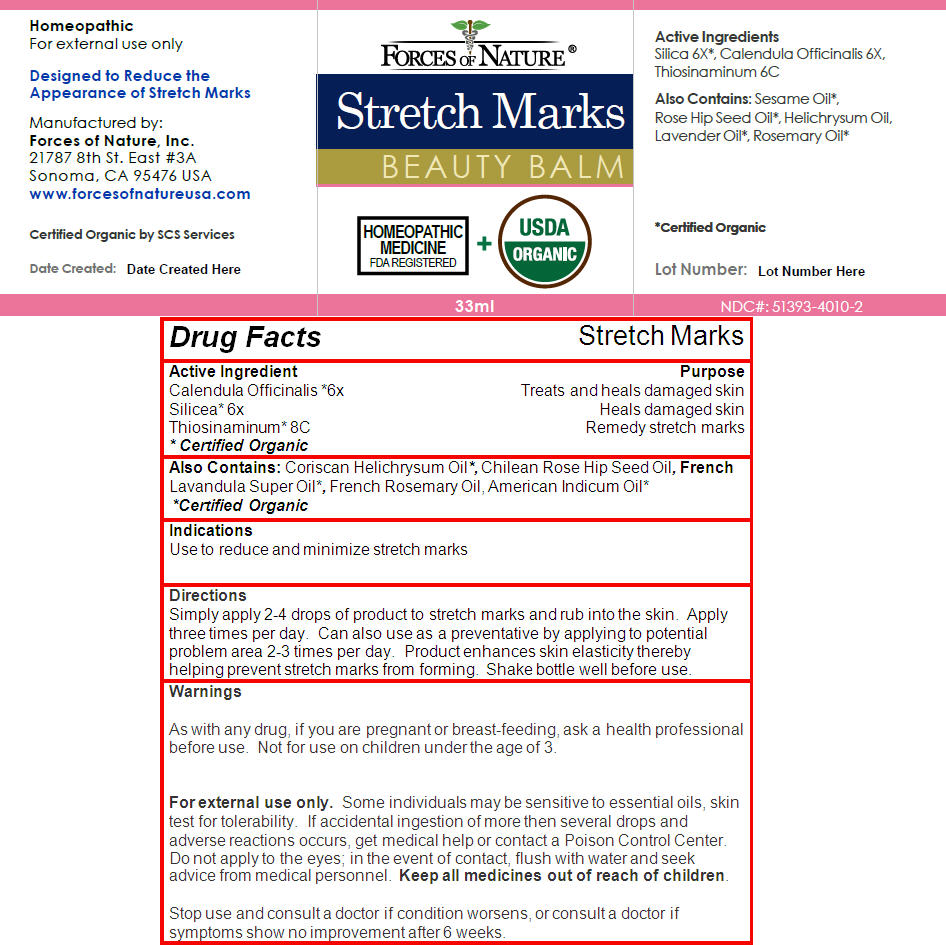 DRUG LABEL: Stretch Mark Control
NDC: 51393-4010 | Form: SOLUTION/ DROPS
Manufacturer: Forces of Nature
Category: homeopathic | Type: HUMAN OTC DRUG LABEL
Date: 20131218

ACTIVE INGREDIENTS: Calendula Officinalis Flower 6 [hp_X]/100 mL; Hydrated Silica 6 [hp_X]/100 mL; Allylthiourea 8 [hp_C]/100 mL
INACTIVE INGREDIENTS: Helichrysum Italicum Flower Oil; Rosa Canina Fruit Oil; Lavender Oil; Rosemary Oil; Sesame Oil

Stretch Mark Control

Drug Facts

ACTIVE INGREDIENT

Active Ingredient | Purpose
Calendula Officinalis [Certified Organic] 6x | Treats and heals damaged skin
Silicea 6x | Heals damaged skin
Thiosinaminum 8C | Remedy stretch marks

Also Contains

Coriscan Helichrysum Oil [Certified Organic] , Chilean Rose Hip Seed Oil, French Lavandula Super Oil, French Rosemary Oil, American Indicum Oil

Indications

Use to reduce and minimize stretch marks

Directions

Simply apply 2-4 drops of product to stretch marks and rub into the skin. Apply three times per day. Can also use as a preventative by applying to potential problem area 2-3 times per day. Product enhances skin elasticity thereby helping prevent stretch marks from forming. Shake bottle well before use.

Warnings

PREGNANCY OR BREAST FEEDING

As with any drug, if you are pregnant or breast-feeding, ask a health professional before use. Not for use on children under the age of 3.

For external use only. Some individuals may be sensitive to essential oils, skin test for tolerability. If accidental ingestion of more then several drops and adverse reactions occurs, get medical help or contact a Poison Control Center.

DO NOT USE

Do not apply to the eyes; in the event of contact, flush with water and seek advice from medical personnel.

Keep all medicines out of reach of children.

Stop use and consult a doctor if condition worsens, or consult a doctor if symptoms show no improvement after 6 weeks.

Manufactured by:
Forces of Nature, Inc.
21787 8th St. East #3A
Sonoma, CA 95476 USA

PRINCIPAL DISPLAY PANEL - 33 ml Bottle Label

FORCES OF NATURE ®

Stretch Marks

BEAUTY BALM

HOMEOPATHIC
MEDICINE
FDA REGISTERED

+

USDA
ORGANIC

33ml